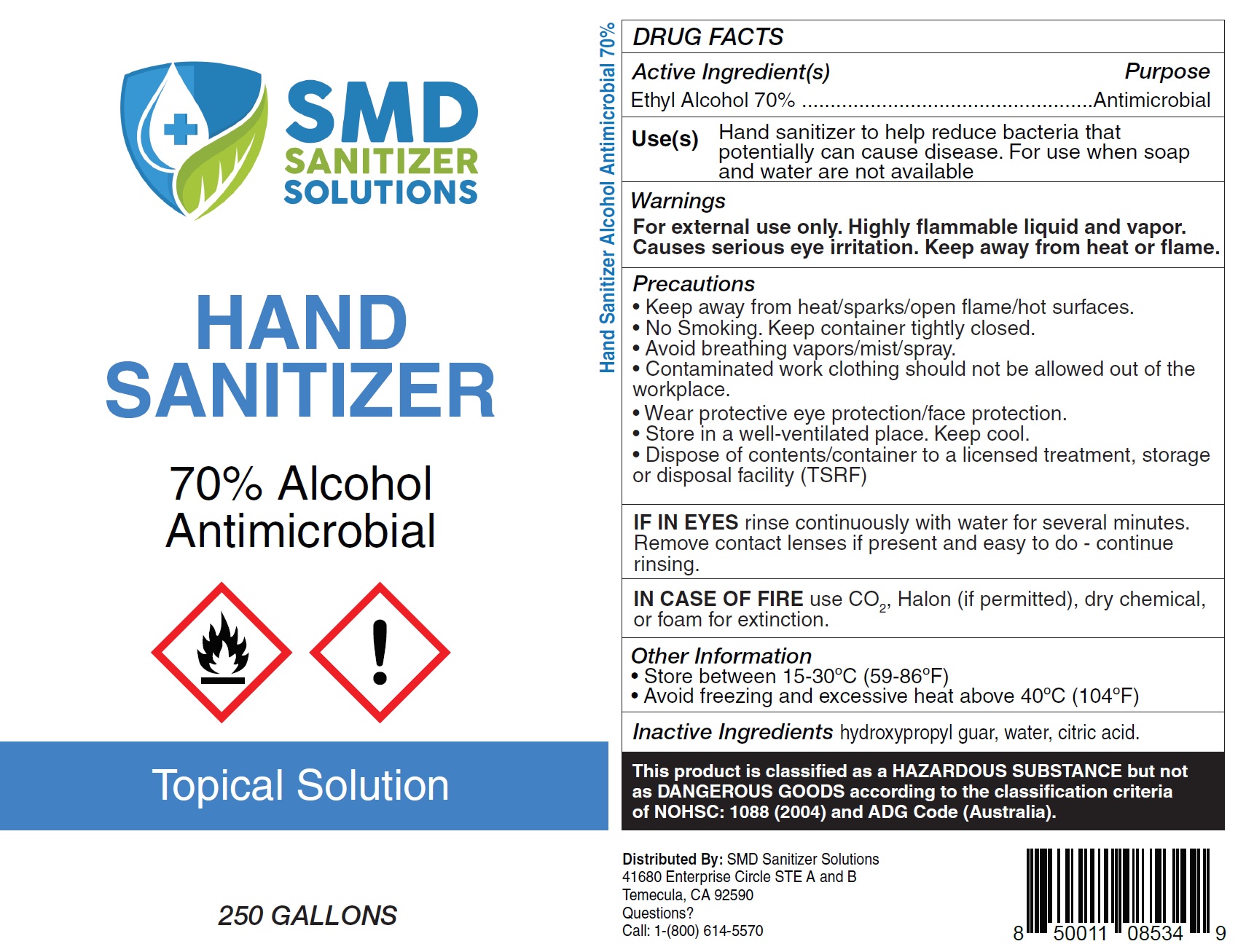 DRUG LABEL: SMD SANITIZER SOLUTIONS HAND SANITIZER
NDC: 73787-115 | Form: GEL
Manufacturer: FGD, LLC
Category: otc | Type: HUMAN OTC DRUG LABEL
Date: 20210106

ACTIVE INGREDIENTS: ALCOHOL 70 mL/100 mL
INACTIVE INGREDIENTS: WATER; CARBOMER INTERPOLYMER TYPE B (ALLYL PENTAERYTHRITOL CROSSLINKED); GLYCERIN; PROPYLENE GLYCOL

SMD SANITIZER SOLUTIONS HAND SANITIZER (250 gallons)

Active ingredient

Ethyl Alcohol 70%

Purpose

Antimicrobial

Uses

Hand sanitizer to help reduce bacteria that potentially can cause disease. For use when soap and water are not available.

Warnings

For external use only

Do Not Use

- In children less than 2 months of age
- On open skin wounds

When using this product keep out of eyes, ears, and mouth.
In case of contact with eyes, rinse eyes thoroughly with water.

Stop use or ask a doctor if irritation or rash occurs.
These may be signs of a serious condition.

Keep out of reach of children

If swallowed, get medical help or contact a Poison Control Center right away.

Directions

- Place enough product on hands to cover all surfaces. Rub hands together until dry.
- Supervise children under 6 years of age when using product to avoid swallowing.

Other Information

- Store between 15-30^0C (59-86^0F)
- Avoid freezing and excessive heat above 40^0C (104^0F)

Inactive ingredients

Carbapol 20, glycerin, proylene glycol, water